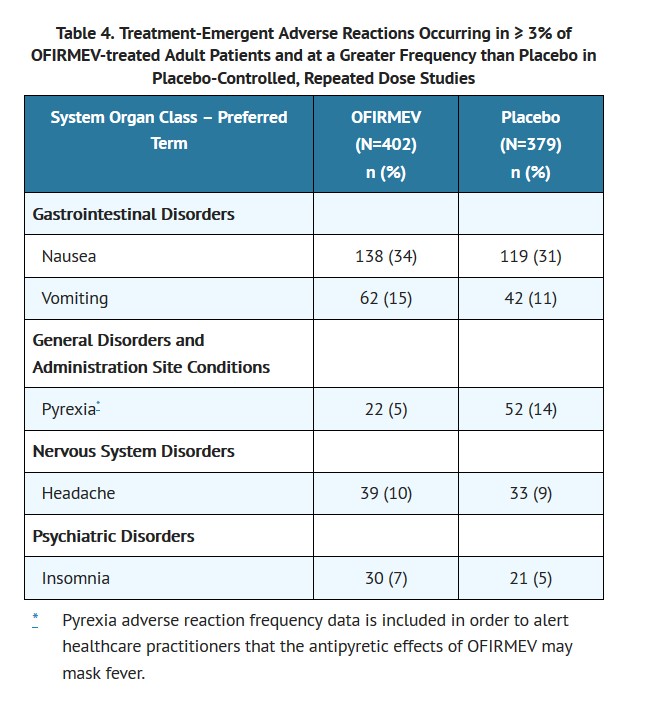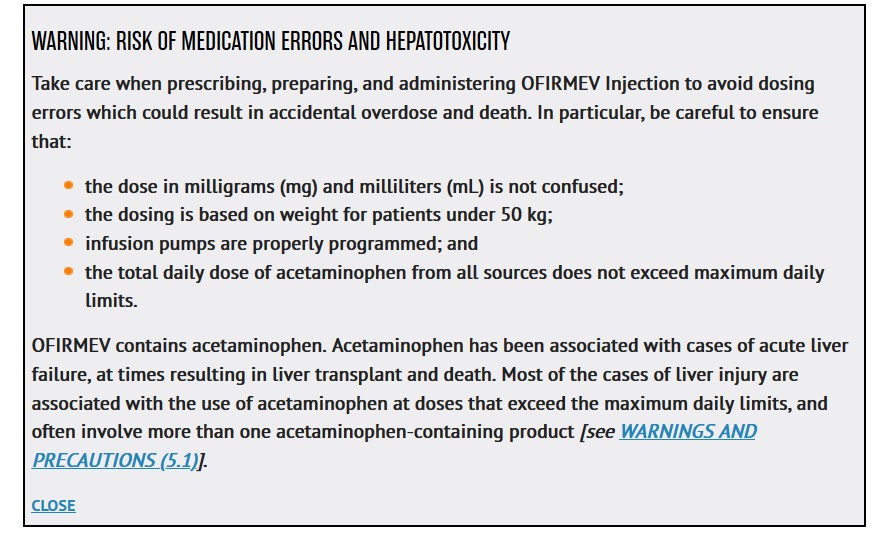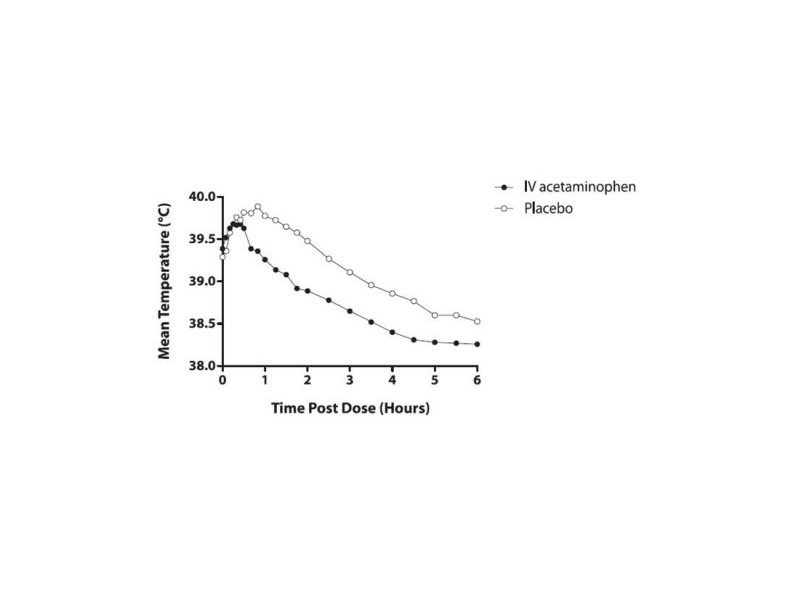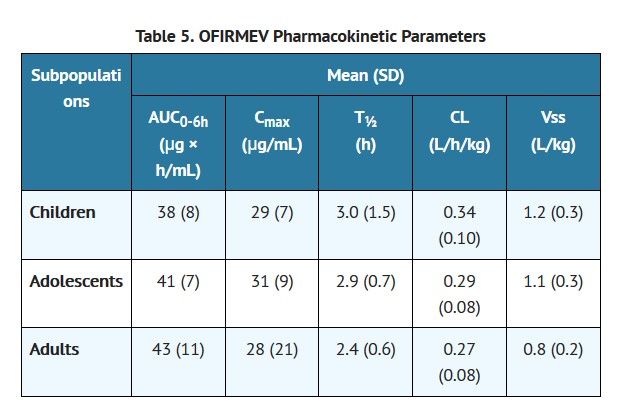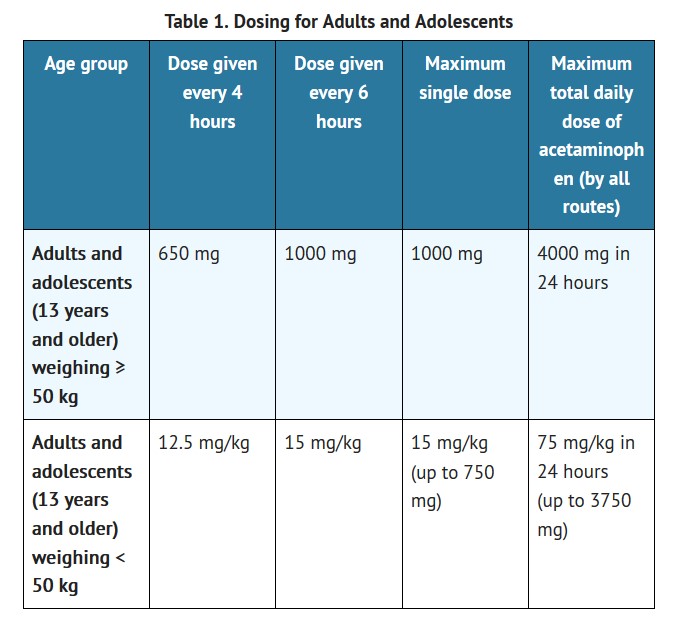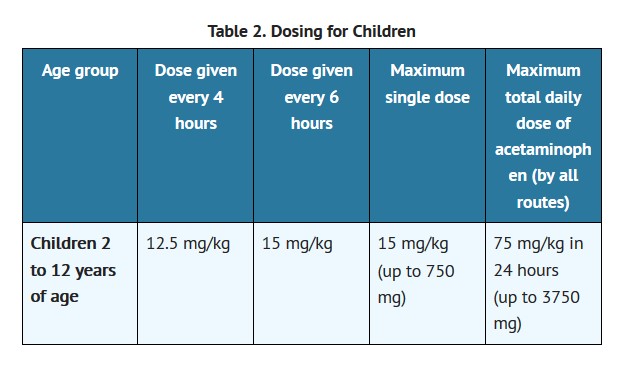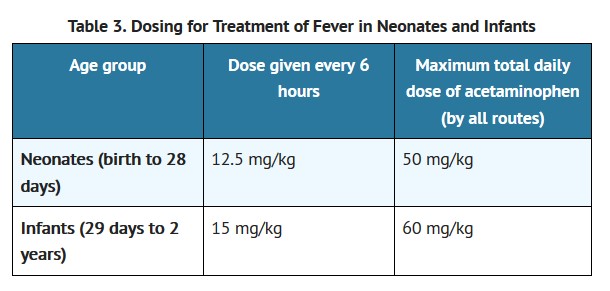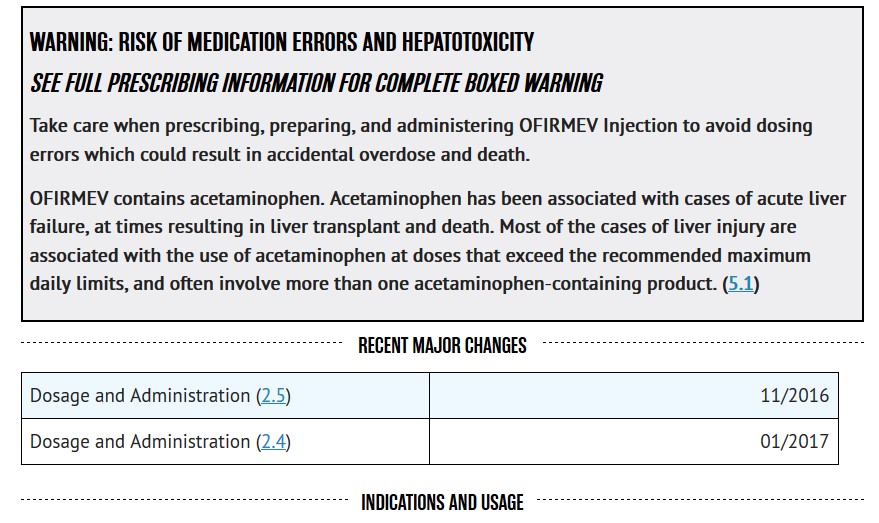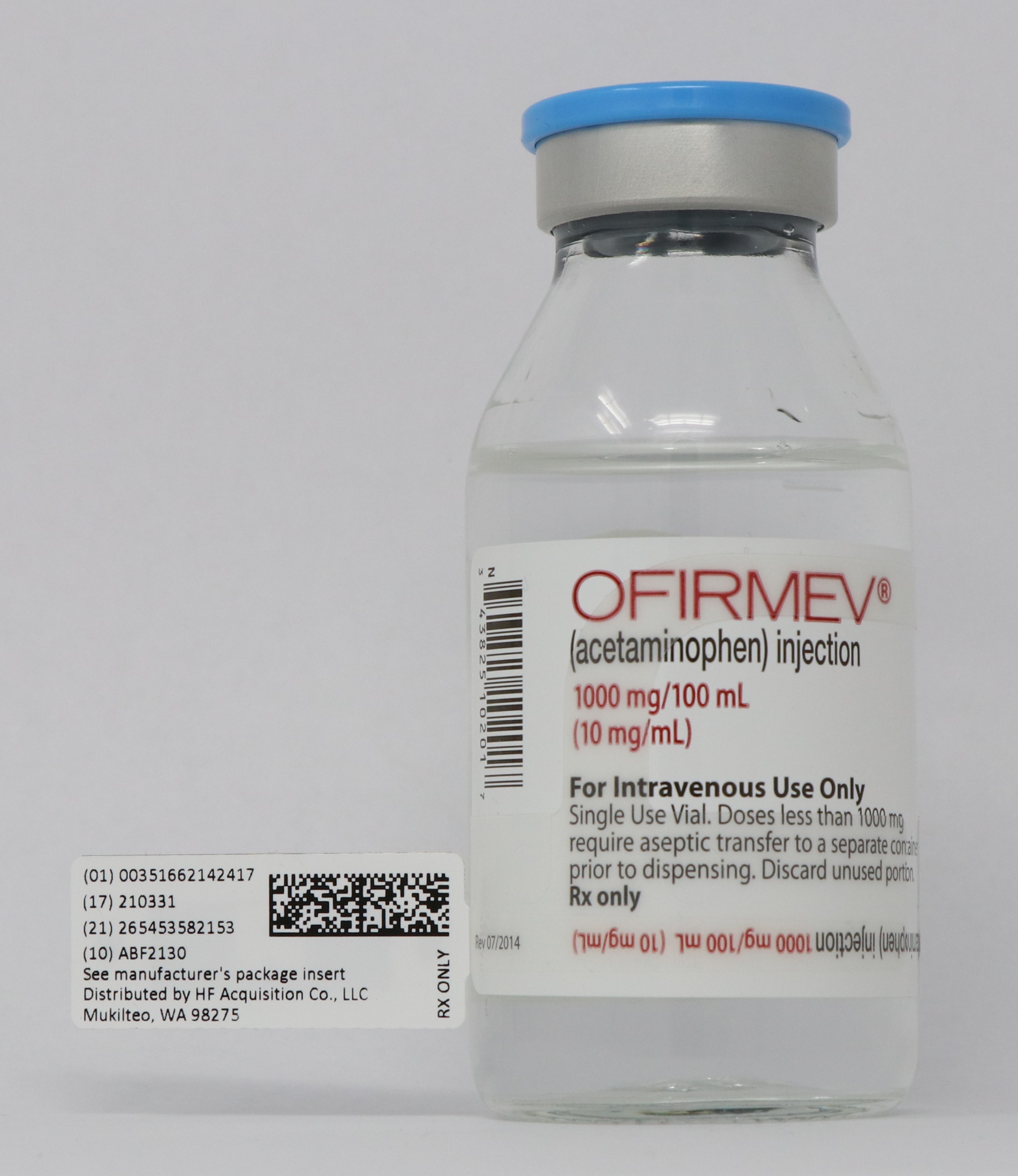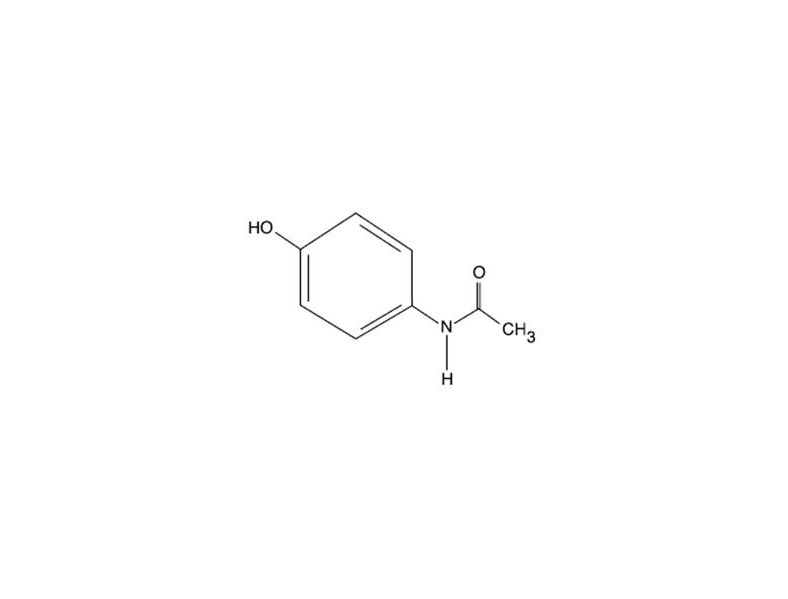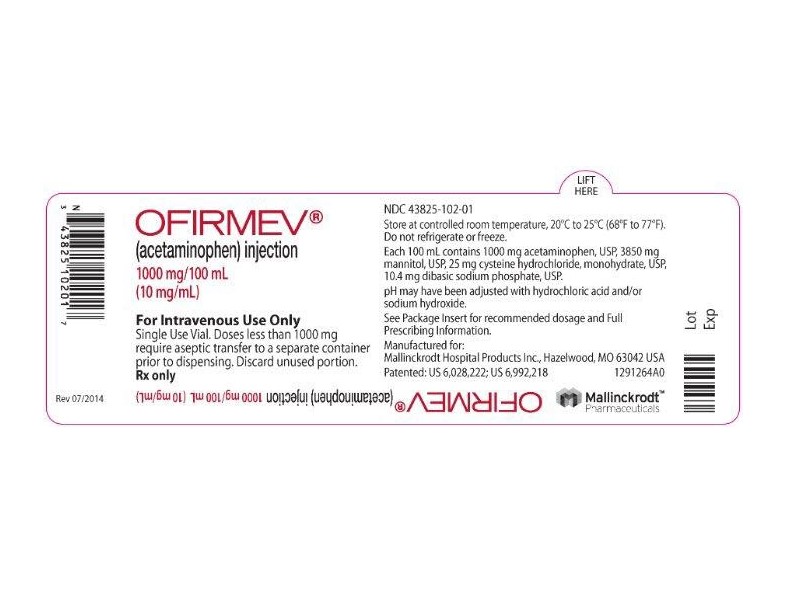 DRUG LABEL: OFIRMEV (ACETAMINOPHEN)
NDC: 51662-1424 | Form: INJECTION, SOLUTION
Manufacturer: HF Acquisition Co LLC, DBA HealthFirst
Category: prescription | Type: HUMAN PRESCRIPTION DRUG LABEL
Date: 20200222

ACTIVE INGREDIENTS: ACETAMINOPHEN 10 mg/1 mL
INACTIVE INGREDIENTS: SODIUM PHOSPHATE, DIBASIC, UNSPECIFIED FORM; SODIUM HYDROXIDE; HYDROCHLORIC ACID; WATER; NITROGEN; MANNITOL; CYSTEINE HYDROCHLORIDE

OFIRMEV (ACETAMINOPHEN) INJECTION 1000mg/100mL (10mg/mL) 100mL VIAL

HIGHLIGHTS OF PRESCRIBING INFORMATION

These highlights do not include all the information needed to use OFIRMEV® safely and effectively. See full prescribing information for OFIRMEV.
OFIRMEV (acetaminophen) Injection
Initial U.S. Approval: 1951

OFIRMEV (acetaminophen) injection is indicated for the

Management of mild to moderate pain in adult and pediatric patients 2 years and older (1)
Management of moderate to severe pain with adjunctive opioid analgesics in adult and pediatric patients 2 years and older (1)
Reduction of fever in adult and pediatric patients (1)

DOSAGE AND ADMINISTRATION

OFIRMEV may be given as a single or repeated dose. (2-2.1)
OFIRMEV should be administered only as a 15-minute intravenous infusion. (2-2.4)

Adults and Adolescents Weighing 50 kg and Over:

1000 mg every 6 hours or 650 mg every 4 hours to a maximum of 4000 mg per day. Minimum dosing interval of 4 hours. (2-2.2)

Adults and Adolescents Weighing Under 50 kg:

15 mg/kg every 6 hours or 12.5 mg/kg every 4 hours to a maximum of 75 mg/kg per day. Minimum dosing interval of 4 hours. (2-2.2)

Children:

Children 2 to 12 years of age: 15 mg/kg every 6 hours or 12.5 mg/kg every 4 hours to a maximum of 75 mg/kg per day. Minimum dosing interval of 4 hours. (2-2.3)

Neonates and Infants:

Neonates including premature neonates born at ≥ 32 weeks gestational age to 28 days chronological age, 12.5 mg/kg every 6 hours to a maximum of 50 mg/kg per day. Minimum dosing interval of 6 hours. (2-2.4)
Infants (29 days to 2 years of age): 15 mg/kg every 6 hours to a maximum of 60 mg/kg per day. Minimum dosing interval of 6 hours. (2-2.4)

DOSAGE FORMS AND STRENGTHS

Injection for intravenous infusion.
Each 100 mL glass vial or bag contains 1000 mg acetaminophen (10 mg/mL). (3)

CONTRAINDICATIONS

Acetaminophen is contraindicated:

In patients with known hypersensitivity to acetaminophen or to any of the excipients in the IV formulation. (4)
In patients with severe hepatic impairment or severe active liver disease. (4)

WARNINGS AND PRECAUTIONS

Administration of acetaminophen in doses higher than recommended (by all routes of administration and from all acetaminophen-containing products including combination products) may result in hepatic injury, including the risk of liver failure and death. (5-5.1)
Use caution when administering acetaminophen in patients with the following conditions: hepatic impairment or active hepatic disease, in cases of alcoholism, chronic malnutrition, severe hypovolemia, or severe renal impairment (creatinine clearance ≤ 30 mL/min). (5-5.1)
Discontinue OFIRMEV immediately at the first appearance of skin rash and if symptoms associated with allergy or hypersensitivity occur. Do not use in patients with acetaminophen allergy. (5-5.2, 5-5.4)
Take care when prescribing, preparing, and administering OFIRMEV injection to avoid dosing errors which could result in accidental overdose and death. (5-5.3)

ADVERSE REACTIONS

The most common adverse reactions in patients treated with OFIRMEV were nausea, vomiting, headache, and insomnia in adult patients; nausea, vomiting, constipation, and pruritus in pediatric patients. (6-6.1)

To report SUSPECTED ADVERSE REACTIONS, contact Mallinckrodt Hospital Products Inc. at 1-800-778-7898 or FDA at 1-800-FDA-1088 or www.fda.gov/medwatch.

DRUG INTERACTIONS

Substances that induce or regulate hepatic cytochrome enzyme CYP2E1 may alter the metabolism of acetaminophen and increase its hepatotoxic potential. (7-7.1)
Chronic oral acetaminophen use at a dose of 4000 mg/day has been shown to cause an increase in international normalized ratio (INR) in some patients who have been stabilized on sodium warfarin as an anticoagulant. (7-7.2)

USE IN SPECIFIC POPULATIONS

Pediatric Use: The effectiveness of OFIRMEV for the treatment of acute pain in pediatric patients younger than 2 years of age has not been established. The safety and effectiveness of OFIRMEV in pediatric patients is supported by evidence from adequate and well controlled studies in adults with additional safety and pharmacokinetic data for this age group. (8-8.4)
Geriatric Use: No overall differences in safety or effectiveness were observed between geriatric and younger subjects. (8-8.5)
Hepatic Impairment: OFIRMEV is contraindicated in patients with severe hepatic impairment or severe active liver disease and should be used with caution in patients with hepatic impairment or active liver disease. (4, 5-5.1, 8-8.6)
Renal Impairment: In cases of severe renal impairment, longer dosing intervals and a reduced total daily dose of acetaminophen may be warranted. (5-5.1, 8-8.7)

Revised: 3/2018

1 INDICATIONS & USAGE

OFIRMEV® (acetaminophen) injection is indicated for

the management of mild to moderate pain in adult and pediatric patients 2 years and older
the management of moderate to severe pain with adjunctive opioid analgesics in adult and pediatric patients 2 years and older
the reduction of fever in adult and pediatric patients.

2 DOSAGE & ADMINISTRATION

2.1 General Dosing Information

OFIRMEV may be given as a single or repeated dose for the treatment of acute pain or fever. No dose adjustment is required when converting between oral acetaminophen and OFIRMEV dosing in adults and adolescents who weigh 50 kg and above. Calculated maximum daily dose of acetaminophen is based on all routes of administration (i.e., intravenous, oral, and rectal) and all products containing acetaminophen. Exceeding the maximum mg/kg daily dose of acetaminophen as described in Tables 1-3 may result in hepatic injury, including the risk of liver failure and death. To avoid the risk of overdose, ensure that the total amount of acetaminophen from all routes and from all sources does not exceed the maximum recommended dose.

2.2 Recommended Dosage: Adults and Adolescents

Adults and adolescents weighing 50 kg and over: the recommended dosage of OFIRMEV is 1000 mg every 6 hours or 650 mg every 4 hours, with a maximum single dose of OFIRMEV of 1000 mg, a minimum dosing interval of 4 hours, and a maximum daily dose of acetaminophen of 4000 mg per day (includes all routes of administration and all acetaminophen-containing products including combination products).

Adults and adolescents weighing under 50 kg: the recommended dosage of OFIRMEV is 15 mg/kg every 6 hours or 12.5 mg/kg every 4 hours, with a maximum single dose of OFIRMEV of 15 mg/kg, a minimum dosing interval of 4 hours, and a maximum daily dose of acetaminophen of 75 mg/kg per day (includes all routes of administration and all acetaminophen-containing products including combination products).

2.3 Recommended Dosage: Children

Children 2 to 12 years of age: the recommended dosage of OFIRMEV is 15 mg/kg every 6 hours or 12.5 mg/kg every 4 hours, with a maximum single dose of OFIRMEV of 15 mg/kg, a minimum dosing interval of 4 hours, and a maximum daily dose of acetaminophen of 75 mg/kg per day.

2.4 Recommended Dosage For Treatment of Fever in Neonates and Infants

Neonates, including premature neonates born at ≥ 32 weeks gestational age, up to 28 days chronological age: the recommended dosage of OFIRMEV is 12.5 mg/kg every 6 hours, to a maximum daily dose of acetaminophen of 50 mg/kg per day, with a minimum dosing interval of 6 hours.

Infants 29 days to 2 years of age: the recommended dosage of OFIRMEV is 15 mg/kg every 6 hours, to a maximum daily dose of acetaminophen of 60 mg/kg per day, with a minimum dosing interval of 6 hours.

2.5 Instructions for Intravenous Administration

For adult and adolescent patients weighing ≥ 50 kg requiring 1000 mg doses of OFIRMEV, administer the dose by inserting a vented intravenous set through the septum of the 100 mL vial or a non-vented intravenous set through the administration spike port of the 100 mL bag. OFIRMEV may be administered without further dilution. Examine the container contents before dose preparation or administering. DO NOT USE if particulate matter or discoloration is observed. Administer the contents of the container intravenously over 15 minutes. Use aseptic technique when preparing OFIRMEV for intravenous infusion. Do not add other medications to the OFIRMEV vial or infusion device.

For doses less than 1000 mg, the appropriate dose must be withdrawn from the container and placed into a separate container prior to administration. Using aseptic technique, withdraw the appropriate dose (650 mg or weight-based) from an intact sealed OFIRMEV container and place the measured dose in a separate empty, sterile container (e.g., glass bottle, plastic intravenous container, or syringe) for intravenous infusion to avoid the inadvertent delivery and administration of the total volume of the commercially available container. The entire 100 mL container of OFIRMEV is not intended for use in patients weighing less than 50 kg. OFIRMEV is supplied in a single-dose container and the unused portion must be discarded.

Place small volume pediatric doses up to 60 mL in volume in a syringe and administer over 15 minutes using a syringe pump.

Monitor the end of the infusion in order to prevent the possibility of an air embolism, especially in cases where the OFIRMEV infusion is the primary infusion.

Once the container seal has been penetrated, or the contents transferred to another container, administer the dose of OFIRMEV within 6 hours.

For bags, refrain from applying excessive pressure causing distortion to the bag, such as wringing or twisting, since such handling could result in breakage of the bag.

Do not add other medications to the OFIRMEV solution. Diazepam and chlorpromazine hydrochloride are physically incompatible with OFIRMEV, therefore do not administer simultaneously.

3 DOSAGE FORMS & STRENGTHS

OFIRMEV is a sterile, clear, colorless, non-pyrogenic, preservative free, isotonic formulation of acetaminophen intended for intravenous infusion. Each 100 mL glass vial or 100 mL bag contains 1000 mg acetaminophen (10 mg/mL).

4 CONTRAINDICATIONS

Acetaminophen is contraindicated:

in patients with known hypersensitivity to acetaminophen or to any of the excipients in the intravenous formulation.
in patients with severe hepatic impairment or severe active liver disease [see Warnings and Precautions (5.1)].

5 WARNINGS AND PRECAUTIONS

5.1 Hepatic Injury

Administration of acetaminophen in doses higher than recommended may result in hepatic injury, including the risk of liver failure and death [see Overdosage (10)]. Do not exceed the maximum recommended daily dose of acetaminophen [see Dosage and Administration (2)]. The maximum recommended daily dose of acetaminophen includes all routes of acetaminophen administration and all acetaminophen-containing products administered, including combination products.

Use caution when administering acetaminophen in patients with the following conditions: hepatic impairment or active hepatic disease, alcoholism, chronic malnutrition, severe hypovolemia (e.g., due to dehydration or blood loss), or severe renal impairment (creatinine clearance ≤ 30 mL/min) [see Use in Specific Populations (8.6, 8.7)].

5.2 Serious Skin Reactions

Rarely, acetaminophen may cause serious skin reactions such as acute generalized exanthematous pustulosis (AGEP), Stevens-Johnson Syndrome (SJS), and toxic epidermal necrolysis (TEN), which can be fatal. Patients should be informed about the signs of serious skin reactions, and use of the drug should be discontinued at the first appearance of skin rash or any other sign of hypersensitivity.

5.3 Risk of Medication Errors

Take care when prescribing, preparing, and administering OFIRMEV (acetaminophen) Injection in order to avoid dosing errors which could result in accidental overdose and death. In particular, be careful to ensure that:

the dose in milligrams (mg) and milliliters (mL) is not confused;
the dosing is based on weight for patients under 50 kg;
infusion pumps are properly programmed; and
the total daily dose of acetaminophen from all sources does not exceed maximum daily limits [see Dosage and Administration (2)].

5.4 Allergy and Hypersensitivity

There have been post-marketing reports of hypersensitivity and anaphylaxis associated with the use of acetaminophen. Clinical signs included swelling of the face, mouth, and throat, respiratory distress, urticaria, rash, and pruritus. There were infrequent reports of life-threatening anaphylaxis requiring emergent medical attention. Discontinue OFIRMEV immediately if symptoms associated with allergy or hypersensitivity occur. Do not use OFIRMEV in patients with acetaminophen allergy.

6 ADVERSE REACTIONS

The following serious adverse reactions are discussed elsewhere in the labeling:

Hepatic Injury [see Warnings and Precautions (5.1)]
Serious Skin Reactions [see Warnings and Precautions (5.2)]
Allergy and Hypersensitivity [see Warnings and Precautions (5.4)]

6.1 Clinical Trial Experience

Because clinical trials are conducted under widely varying conditions, adverse reaction rates observed cannot be directly compared to rates in other clinical trials and may not reflect the rates observed in practice.

Adult Population

A total of 1020 adult patients have received OFIRMEV in clinical trials, including 37.3% (n=380) who received 5 or more doses, and 17.0% (n=173) who received more than 10 doses. Most patients were treated with OFIRMEV 1000 mg every 6 hours. A total of 13.1% (n=134) received OFIRMEV 650 mg every 4 hours.

All adverse reactions that occurred in adult patients treated with either OFIRMEV or placebo in repeated dose, placebo-controlled clinical trials at an incidence ≥ 3% and at a greater frequency than placebo are listed in Table 4. The most common adverse events in adult patients treated with OFIRMEV (incidence ≥ 5% and greater than placebo) were nausea, vomiting, headache, and insomnia.

Other Adverse Reactions Observed During Clinical Studies of OFIRMEV in Adults

The following additional treatment-emergent adverse reactions were reported by adult subjects treated with OFIRMEV in all clinical trials (n=1020) that occurred with an incidence of at least 1% and at a frequency greater than placebo (n=525).

Blood and lymphatic system disorders: anemia

General disorders and administration site conditions: fatigue, infusion site pain, edema peripheral

Investigations: aspartate aminotransferase increased, breath sounds abnormal

Metabolism and nutrition disorders: hypokalemia

Musculoskeletal and connective tissue disorders: muscle spasms, trismus

Psychiatric disorders: anxiety

Respiratory, thoracic and mediastinal disorders: dyspnea

Vascular disorders: hypertension, hypotension

Pediatric Population

A total of 483 pediatric patients (72 neonates, 167 infants, 171 children, and 73 adolescents) have received OFIRMEV in active-controlled (n=250) and open-label clinical trials (n=225), including 43.9% (n=212) who received 5 or more doses and 31.2% (n=153) who received more than 10 doses. Pediatric patients received OFIRMEV doses up to 15 mg/kg on an every 4 hours, every 6 hours, or every 8 hours schedule. The maximum exposure was 7.7, 6.4, 6.8, and 7.1 days in neonates, infants, children, and adolescents, respectively.

The most common adverse events (incidence ≥ 5%) in pediatric patients treated with OFIRMEV were nausea, vomiting, constipation, and pruritus.

Other Adverse Reactions Observed During Clinical Studies of OFIRMEV in Pediatrics

The following additional treatment-emergent adverse reactions were reported by pediatric subjects treated with OFIRMEV (n=483) that occurred with an incidence of at least 1%.

Blood and lymphatic system disorders: anemia

Gastrointestinal disorders: diarrhea

General disorders and administration site conditions: pyrexia, injection site pain

Metabolism and nutrition disorders: hypokalemia, hypomagnesemia, hypoalbuminemia, hypophosphatemia

Musculoskeletal and connective tissue disorders: muscle spasm

Nervous system disorders: headache

Psychiatric disorders: agitation

Renal and urinary disorders: oliguria

Respiratory, thoracic and mediastinal disorders: atelectasis, pleural effusion, pulmonary edema, stridor, wheezing

Vascular disorders: hypotension, hypertension

7 DRUG INTERACTIONS

7.1 Effects of Other Substances on Acetaminophen

Substances that induce or regulate hepatic cytochrome enzyme CYP2E1 may alter the metabolism of acetaminophen and increase its hepatotoxic potential. The clinical consequences of these effects have not been established. Effects of ethanol are complex, because excessive alcohol usage can induce hepatic cytochromes, but ethanol also acts as a competitive inhibitor of the metabolism of acetaminophen.

7.2 Anticoagulants

Chronic oral acetaminophen use at a dose of 4000 mg/day has been shown to cause an increase in international normalized ratio (INR) in some patients who have been stabilized on sodium warfarin as an anticoagulant. As no studies have been performed evaluating the short-term use of OFIRMEV in patients on oral anticoagulants, more frequent assessment of INR may be appropriate in such circumstances.

8 USE IN SPECIFIC POPULATIONS

Risk Summary

Published epidemiological studies with oral acetaminophen use during pregnancy have not reported a clear association with acetaminophen use and birth defects, miscarriage, or adverse maternal or fetal outcomes [see Data]. Animal reproduction studies have not been conducted with IV acetaminophen. Reproductive and developmental studies in rats and mice from the published literature identified adverse events at clinically relevant doses with acetaminophen. Treatment of pregnant rats with doses of acetaminophen approximately equal to the maximum human daily dose (MHDD) showed evidence of fetotoxicity and increases in bone variations in the fetuses. In another study, necrosis was observed in the liver and kidney of both pregnant rats and fetuses at doses approximately equal to the MHDD. In mice and rats treated with acetaminophen at doses within the clinical dosing range, cumulative adverse effects on reproductive capacity were reported. In mice, a reduction in number of litters of the parental mating pair was observed as well as retarded growth, abnormal sperm in their offspring and reduced birth weight in the next generation. In rats, female fertility was decreased following in utero exposure to acetaminophen [see Data].

The estimated background risk of major birth defects and miscarriages for the indicated population is unknown. All pregnancies have a background risk of birth defect, loss, or other adverse outcomes. In the U.S. general population, the estimated background risk of major birth defects and miscarriage in clinically recognized pregnancies is 2-4% and 15-20%, respectively.

Data

Human Data

The results from a large population-based prospective cohort, including data from 26,424 women with live born singletons who were exposed to oral acetaminophen during the first trimester, indicate no increased risk for congenital malformations, compared to a control group of unexposed children. The rate of congenital malformations (4.3%) was similar to the rate in the general population. A population-based, case-control study from the National Birth Defects Prevention Study showed that 11,610 children with prenatal exposure to acetaminophen during the first trimester had no increased risk of major birth defects compared to 4,500 children in the control group. Other epidemiological data showed similar results. However, these studies cannot definitely establish the absence of any risk because of methodological limitations, including recall bias.

Animal Data

Studies in pregnant rats that received oral acetaminophen during organogenesis at doses up to 0.85 times the maximum human daily dose (MHDD = 4 grams/day, based on a body surface area comparison) showed evidence of fetotoxicity (reduced fetal weight and length) and a dose-related increase in bone variations (reduced ossification and rudimentary rib changes). Offspring had no evidence of external, visceral, or skeletal malformations. When pregnant rats received oral acetaminophen throughout gestation at doses of 1.2 times the MHDD (based on a body surface area comparison), areas of necrosis occurred in both the liver and kidney of pregnant rats and fetuses. These effects did not occur in animals that received oral acetaminophen at doses 0.3 times the MHDD, based on a body surface area comparison.

In a continuous breeding study, pregnant mice received 0.25, 0.5, or 1.0% acetaminophen via the diet (357, 715, or 1430 mg/kg/day). These doses are approximately 0.43, 0.87, and 1.7 times the MHDD, respectively, based on a body surface area comparison. A dose related reduction in body weights of fourth and fifth litter offspring of the treated mating pair occurred during lactation and post-weaning at all doses. Animals in the high dose group had a reduced number of litters per mating pair, male offspring with an increased percentage of abnormal sperm, and reduced birth weights in the next generation pups.

8.2 Lactation

Risk Summary

There is no information regarding the presence of OFIRMEV in human milk, the effects on the breastfed infant, or the effects on milk production. However, limited published studies report that acetaminophen passes rapidly into human milk with similar levels in the milk and plasma. Average and maximum neonatal doses of 1% and 2%, respectively, of the weight-adjusted maternal dose are reported after a single oral administration of 1 gram APAP. There is one well-documented report of a rash in a breast-fed infant that resolved when the mother stopped acetaminophen use and recurred when she resumed acetaminophen use. The developmental and health benefits of breastfeeding should be considered along with the mother's clinical need for OFIRMEV and any potential adverse effects on the breastfed infant from OFIRMEV or from the underlying maternal condition.

8.3 Females and Males of Reproductive Potential

Based on animal data use of acetaminophen may cause reduced fertility in males and females of reproductive potential. It is not known whether these effects on fertility are reversible. Published animal studies reported that oral acetaminophen treatment of male animals at doses that are 1.2 times the MHDD and greater (based on a body surface area comparison) result in decreased testicular weights, reduced spermatogenesis, and reduced fertility. In female animals given the same doses, reduced implantation sites were reported. Additional published animal studies indicate that acetaminophen exposure in utero adversely impacts reproductive capacity of both male and female offspring at clinically relevant exposures [see Nonclinical Toxicology (13.1)].

8.4 Pediatric Use

Treatment of Acute Pain

The safety and effectiveness of OFIRMEV for the treatment of acute pain in pediatric patients ages 2 years and older is supported by evidence from adequate and well-controlled studies of OFIRMEV in adults and safety and pharmacokinetic data from adult and 483 pediatric patients across all age groups [see Dosage and Administration (2.3) and CLINICAL PHARMACOLOGY-Pharmacokinetics (12.3)].

The effectiveness of OFIRMEV for the treatment of acute pain in pediatric patients younger than 2 years of age has not been established.

In patients younger than 2 years, efficacy was not demonstrated in a double-blind, placebo-controlled study of 198 pediatric patients younger than 2 years. Pediatric patients less than 2 years of age, including neonates from 28 to 40 weeks gestational age at birth, were randomized to receive opioid plus acetaminophen or opioid plus placebo. No difference in analgesic effect of intravenous acetaminophen, measured by assessment of reduced need for additional opioid treatment for pain control, was observed.

Treatment of Fever

The safety and effectiveness of OFIRMEV for the treatment of fever in pediatric patients, including premature neonates born at ≥ 32 weeks gestational age is supported by adequate and well-controlled studies of OFIRMEV in adults, clinical studies in 244 pediatric patients 2 years and older, and safety and pharmacokinetic data from 239 patients younger than 2 years including neonates ≥ 32 weeks gestational age.

8.5 Geriatric Use

Of the total number of subjects in clinical studies of OFIRMEV, 15% were age 65 and over, while 5% were age 75 and over. No overall differences in safety or effectiveness were observed between these subjects and younger subjects, and other reported clinical experience has not identified differences in responses between the elderly and younger patients, but greater sensitivity of some older individuals cannot be ruled out.

8.6 Patients with Hepatic Impairment

Acetaminophen is contraindicated in patients with severe hepatic impairment or severe active liver disease and should be used with caution in patients with hepatic impairment or active liver disease [see Warnings and Precautions (5.1) and Clinical Pharmacology (12)]. A reduced total daily dose of acetaminophen may be warranted.

8.7 Patients with Renal Impairment

In cases of severe renal impairment (creatinine clearance ≤ 30 mL/min), longer dosing intervals and a reduced total daily dose of acetaminophen may be warranted.

10 OVERDOSAGE

Signs and Symptoms

In acute acetaminophen overdosage, dose-dependent, potentially fatal hepatic necrosis is the most serious adverse effect. Renal tubular necrosis, hypoglycemic coma, and thrombocytopenia may also occur. Plasma acetaminophen levels > 300 mcg/mL at 4 hours after oral ingestion were associated with hepatic damage in 90% of patients; minimal hepatic damage is anticipated if plasma levels at 4 hours are < 150 mcg/mL or < 37.5 mcg/mL at 12 hours after ingestion. Early symptoms following a potentially hepatotoxic overdose may include: nausea, vomiting, diaphoresis, and general malaise. Clinical and laboratory evidence of hepatic toxicity may not be apparent until 48 to 72 hours post-ingestion.

Treatment

If an acetaminophen overdose is suspected, obtain a serum acetaminophen assay as soon as possible, but no sooner than 4 hours following oral ingestion. Obtain liver function studies initially and repeat at 24-hour intervals. Administer the antidote N-acetylcysteine (NAC) as early as possible. As a guide to treatment of acute ingestion, the acetaminophen level can be plotted against time since oral ingestion on a nomogram (Rumack-Matthew). The lower toxic line on the nomogram is equivalent to 150 mcg/mL at 4 hours and 37.5 mcg/mL at 12 hours. If serum level is above the lower line, administer the entire course of NAC treatment. Withhold NAC therapy if the acetaminophen level is below the lower line.

For additional information, call a poison control center at 1-800-222-1222.

11 DESCRIPTION

Acetaminophen is a non-salicylate antipyretic and non-opioid analgesic agent. Its chemical name is N-acetyl-p-aminophenol. Acetaminophen has a molecular weight of 151.16. Its structural formula is:

OFIRMEV injection is a sterile, clear, colorless, non pyrogenic, isotonic formulation of acetaminophen intended for intravenous infusion. It has a pH of approximately 5.5 and an osmolality of approximately 290 mOsm/kg. Each 100 mL contains 1000 mg acetaminophen, USP, 3850 mg mannitol, USP, 25 mg cysteine hydrochloride, monohydrate, USP, and 10.4 mg dibasic sodium phosphate, USP. pH is adjusted with hydrochloric acid and/or sodium hydroxide.

12 CLINICAL PHARMACOLOGY

12.1 Mechanism of Action

The precise mechanism of the analgesic and antipyretic properties of acetaminophen is not established but is thought to primarily involve central actions.

12.2 Pharmacodynamics

Acetaminophen has been shown to have analgesic and antipyretic activities in animal and human studies.

Single doses of OFIRMEV up to 3000 mg and repeated doses of 1000 mg every 6 hours for 48 hours have not been shown to cause a significant effect on platelet aggregation. Acetaminophen does not have any immediate or delayed effects on small-vessel hemostasis. Clinical studies of both healthy subjects and patients with hemophilia showed no significant changes in bleeding time after receiving multiple doses of oral acetaminophen.

12.3 Pharmacokinetics

Distribution

The pharmacokinetics of OFIRMEV have been studied in patients and healthy subjects up to 60 years old. The pharmacokinetic profile of OFIRMEV has been demonstrated to be dose proportional in adults following administration of single doses of 500, 650, and 1000 mg.

The maximum concentration (Cmax) occurs at the end of the 15-minute intravenous infusion of OFIRMEV. Compared to the same dose of oral acetaminophen, the Cmax following administration of OFIRMEV is up to 70% higher, while overall exposure (area under the concentration time curve [AUC]) is very similar.

Pharmacokinetic parameters of OFIRMEV (AUC, Cmax, terminal elimination half-life [T½], systemic clearance [CL], and volume of distribution at steady state [Vss]) following administration of a single intravenous dose of 15 mg/kg in children and adolescents and 1000 mg in adults are summarized in Table 5.

The concentrations of acetaminophen observed in neonates greater than 32 weeks gestational age at birth treated with 12.5 mg/kg dose are similar to infants, children and adolescents treated with a 15 mg/kg dose, and similar to adults treated with a 1000 mg dose.

At therapeutic levels, binding of acetaminophen to plasma proteins is low (ranging from 10% to 25%). Acetaminophen appears to be widely distributed throughout most body tissues except fat.

Metabolism and Excretion

Acetaminophen is primarily metabolized in the liver by first-order kinetics and involves three principal separate pathways: Conjugation with glucuronide, conjugation with sulfate, and oxidation via the cytochrome P450 enzyme pathway, primarily CYP2E1, to form a reactive intermediate metabolite (N-acetyl-p-benzoquinone imine or NAPQI). With therapeutic doses, NAPQI undergoes rapid conjugation with glutathione and is then further metabolized to form cysteine and mercapturic acid conjugates.

Acetaminophen metabolites are mainly excreted in the urine. Less than 5% is excreted in the urine as unconjugated (free) acetaminophen and more than 90% of the administered dose is excreted within 24 hours.

13 NONCLINICAL TOXICOLOGY

13.1 Carcinogenesis, Mutagenesis, Impairment of Fertility

Carcinogenesis

Long-term studies in mice and rats have been completed by the National Toxicology Program to evaluate the carcinogenic potential of acetaminophen. In 2-year feeding studies, F344/N rats and B6C3F1 mice were fed a diet containing acetaminophen up to 6000 ppm. Female rats demonstrated equivocal evidence of carcinogenic activity based on increased incidences of mononuclear cell leukemia at 0.8 times the maximum human daily dose (MHDD) of 4 grams/day, based on a body surface area comparison. In contrast, there was no evidence of carcinogenic activity in male rats (0.7 times) or mice (1.2-1.4 times the MHDD, based on a body surface area comparison).

Mutagenesis

Acetaminophen was not mutagenic in the bacterial reverse mutation assay (Ames test). In contrast, acetaminophen tested positive in the in vitro mouse lymphoma assay and the in vitro chromosomal aberration assay using human lymphocytes. In the published literature, acetaminophen has been reported to be clastogenic when administered a dose of 1500 mg/kg/day to the rat model (3.6 times the MHDD, based on a body surface area comparison). In contrast, no clastogenicity was noted at a dose of 750 mg/kg/day (1.8 times the MHDD, based on a body surface area comparison), suggesting a threshold effect.

Impairment of Fertility

In studies conducted by the National Toxicology Program, fertility assessments have been completed in Swiss mice via a continuous breeding study. There were no effects on fertility parameters in mice consuming up to 1.7 times the MHDD of acetaminophen, based on a body surface area comparison. Although there was no effect on sperm motility or sperm density in the epididymis, there was a significant increase in the percentage of abnormal sperm in mice consuming 1.7 times the MHDD (based on a body surface area comparison) and there was a reduction in the number of mating pairs producing a fifth litter at this dose, suggesting the potential for cumulative toxicity with chronic administration of acetaminophen near the upper limit of daily dosing.

Published studies in rodents report that oral acetaminophen treatment of male animals at doses that are 1.2 times the MHDD and greater (based on a body surface area comparison) result in decreased testicular weights, reduced spermatogenesis, reduced fertility, and reduced implantation sites in females given the same doses. These effects appear to increase with the duration of treatment.

In a published mouse study, oral administration of 50 mg/kg acetaminophen to pregnant mice from Gestation Day 7 to delivery (0.06 times the MHDD, based on a body surface area comparison) reduced the number of primordial follicles in female offspring and reduced the percentage of full term pregnancies and number of pups born to these females exposed to acetaminophen in utero.

In a published study, oral administration of 350 mg/kg acetaminophen to pregnant rats (0.85 times the MHDD, based on a body surface area comparison) from Gestation Day 13 to 21 (dams) reduced the number of germ cells in the fetal ovary, decreased ovary weight, and reduced the number of pups per litter in F1 females as well as reduced ovary weights in F2 females.

14 CLINICAL STUDIES

14.1 Adult Acute Pain

The efficacy of OFIRMEV in the treatment of acute pain in adults was evaluated in two randomized, double-blind, placebo-controlled clinical trials in patients with postoperative pain.

Pain Study 1 evaluated the analgesic efficacy of repeated doses of OFIRMEV 1000 mg vs. placebo every 6 hours for 24 hours in 101 patients with moderate to severe pain following total hip or knee replacement. OFIRMEV was statistically superior to placebo for reduction in pain intensity over 24 hours. There was an attendant decrease in opioid consumption, the clinical benefit of which was not demonstrated.

Pain Study 2 evaluated the analgesic efficacy of repeated doses of OFIRMEV 1000 mg every 6 hours or 650 mg every 4 hours for 24 hours versus placebo in the treatment of 244 patients with moderate to severe postoperative pain after abdominal laparoscopic surgery. Patients receiving OFIRMEV experienced a statistically significant greater reduction in pain intensity over 24 hours compared to placebo.

14.2 Adult Fever

The efficacy of OFIRMEV 1000 mg in the treatment of adult fever was evaluated in one randomized, double-blind, placebo-controlled clinical trial. The study was a 6-hour, single-dose, endotoxin-induced fever study in 60 healthy adult males. A statistically significant antipyretic effect of OFIRMEV was demonstrated through 6 hours in comparison to placebo. The mean temperature over time is shown in Figure 1.

Figure 1: Mean Temperature (°C) Over Time

14.3 Pediatric Acute Pain and Fever

OFIRMEV was studied in pediatric patients in three active-controlled trials and three open-label safety and pharmacokinetic trials [see Use in Specific Populations (8.4)].

16 HOW SUPPLIED/STORAGE & HANDLING

OFIRMEV (ACETAMINOPHEN) INJECTION is supplied in the following dosage forms.
NDC 51662-1424-1
OFIRMEV (ACETAMINOPHEN) INJECTION 1000mg/100mL (10mg/mL) 100mL VIAL

HF Acquisition Co LLC, DBA HealthFirst
Mukilteo, WA 98275

Also supplied in the following manufacture supplied dosage forms

NDC 43825-102-01 - OFIRMEV (acetaminophen) Injection is supplied in a 100 mL glass vial containing 1000 mg acetaminophen (10 mg/mL) in cartons of 24 vials.

NDC 43825-102-03 - OFIRMEV (acetaminophen) Injection is supplied in a 100 mL bag containing 1000 mg acetaminophen (10 mg/mL) in cartons of 24 bags.

Do not remove unit from overwrap until ready for use.

To open, tear outer wrap at the notch and remove solution bag. After removing the outer wrap, check the container for minute leaks by squeezing the solution bag firmly. If leaks are found, discard the solution because the sterility may be impaired. A small amount of moisture may be present inside the outer wrap.

OFIRMEV should be stored at 20°C to 25°C (68°F to 77°F) [see USP Controlled Room Temperature].

For single-dose only. The product should be used within 6 hours after opening. Do not refrigerate or freeze.

SPL UNCLASSIFIED

Manufactured for:
Mallinckrodt Hospital Products Inc.
Hazelwood, MO 63042 USA

Revised: 03/2018

Mallinckrodt, the "M" brand mark, the Mallinckrodt Pharmaceuticals logo and other brands are trademarks of a Mallinckrodt company.

© 2018 Mallinckrodt.

U.S. PATENT NUMBERS:
6,028,222; 6,992,218

Mallinckrodt™
Pharmaceuticals